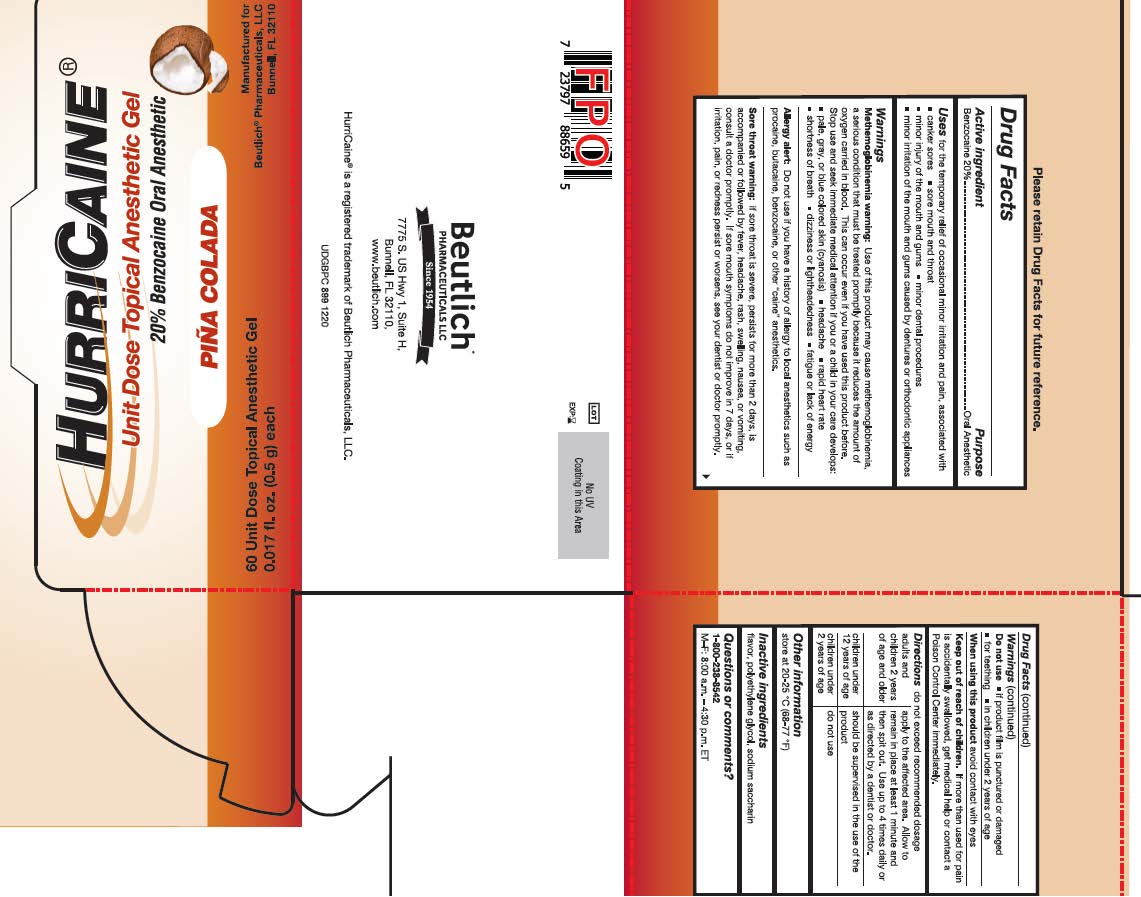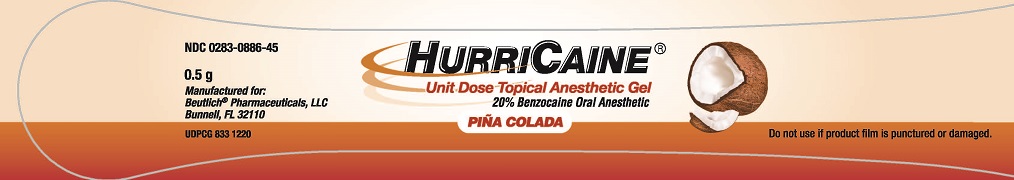 DRUG LABEL: HurriCaine
NDC: 0283-0886 | Form: GEL
Manufacturer: Beutlich Pharmaceuticals, LLC
Category: otc | Type: HUMAN OTC DRUG LABEL
Date: 20251106

ACTIVE INGREDIENTS: BENZOCAINE 200 mg/1 g
INACTIVE INGREDIENTS: POLYETHYLENE GLYCOL 400; POLYETHYLENE GLYCOL 3350; SACCHARIN SODIUM

PC Unit Dose Gel
Drug Facts

Active ingredient

Benzocaine 20%

Purpose

Oral Anesthetic

Uses

for the temporary relief of occasional minor irritation and pain associated with:

- canker sores
- sore mouth and throat
- minor injury of the mouth and gums
- minor dental procedures
- minor irritation of the mouth and gums caused by dentures or orthodontic appliances

Warnings

Methemoglobinemia warning:
Use of this product may cause methemoglobinemia, a serious condition that must be treated promptly because it reduces the amount of oxygen carried in blood. This can occur even if you have used this product before. Stop use and seek immediate medical attention if you or a child in your care develops:
• pale, gray, or blue colored skin (cyanosis)
• headache
• rapid heart rate
• shortness of breath
• dizziness or lightheadedness
• fatigue or lack of energy

Allergy alert: Do not use if you have a history of allergy to local anesthetics such as procaine, butacaine, benzocaine or other "caine" anesthetics.

Sore throat warning: If sore throat is severe, persists for more than 2 days, is accompanied or followed by fever, headache, rash, swelling, nausea, or vomiting, consult a doctor promptly. If sore mouth symptoms do not improve in 7 days, or irritation, pain, or redness persists or worsens, see your dentist or doctor promptly.

Do Not Use

• if product film is punctured or damaged
• for teething
• in children under 2 years of age

When using this product: avoid contact with eyes

Keep out of reach of children. If more than used for pain is accidentally swallowed, get medical help or contact a Poison Control Center immediately.

Directions

• do not exceed recommended dosage

adults and children 2 years of age and older: apply to the affected area. Allow to remain in place at least 1 minute and then spit out. Use up to 4 times daily or as directed by a dentist or doctor.

children under 12 years of age: should be supervised in the use of the product

children under 2 years of age: do not use

Storage and Handling

- store at 20°-25°C (68°-77°F)

Inactive ingredients

flavor, polyethylene glycol, sodium saccharin

Questions or comments?

1-800-238-8542
M-F: 8:00 a.m. to 4:30 p.m. ET

Principal Display Panel

HurriCaine Unit Dose Gel Pina Colada 0.5g with Swab: 0283-0886-45

60ct HurriCaine Unit Dose Gel Pina Colada 0.5g with Swab: 0283-0886-59